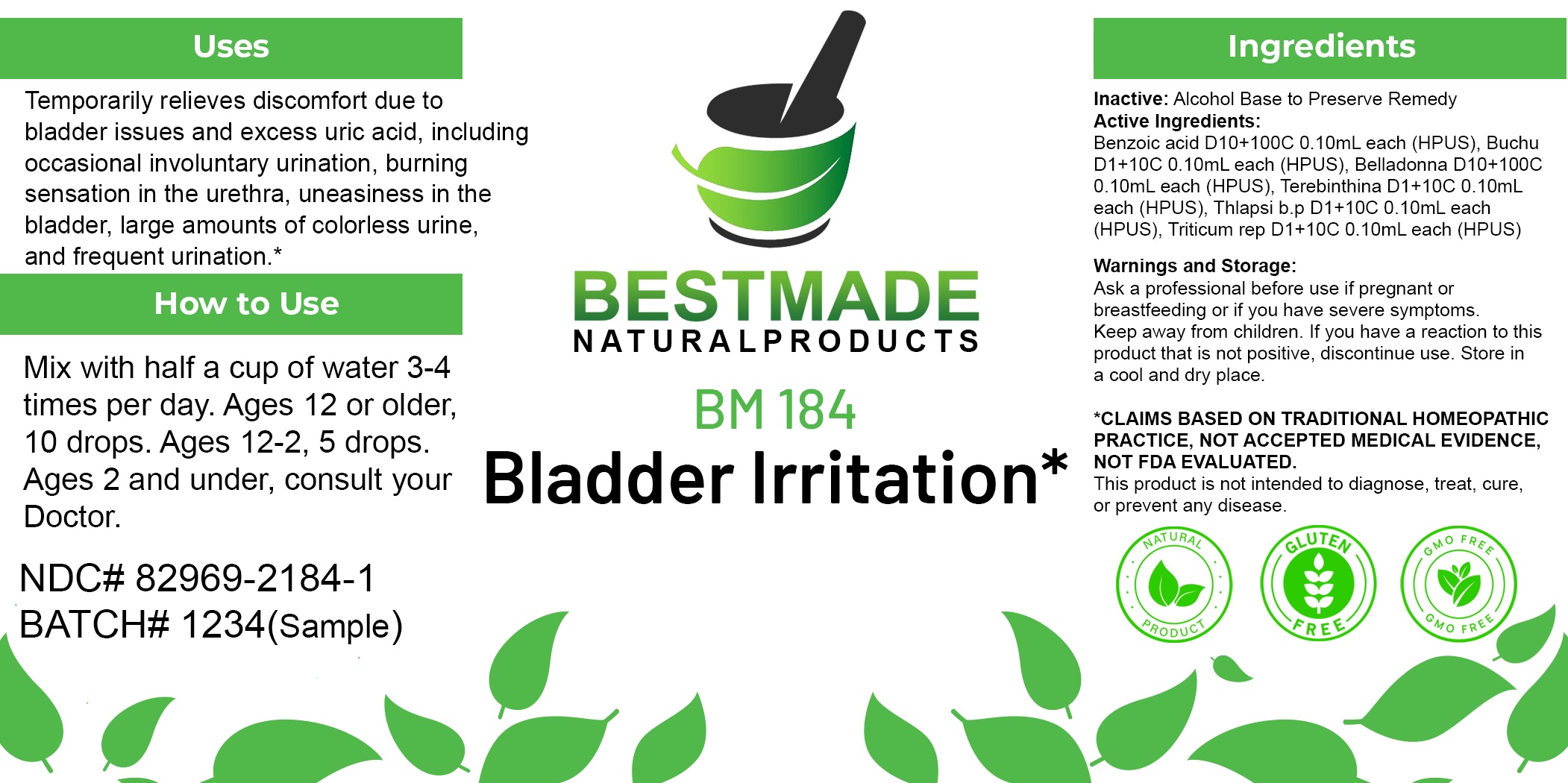 DRUG LABEL: Bestmade Natural Products BM184
NDC: 82969-2184 | Form: LIQUID
Manufacturer: Bestmade Natural Products
Category: homeopathic | Type: HUMAN OTC DRUG LABEL
Date: 20250220

ACTIVE INGREDIENTS: BENZOIC ACID 30 [hp_C]/30 [hp_C]; ELYMUS REPENS ROOT 30 [hp_C]/30 [hp_C]; AGATHOSMA CRENULATA WHOLE 30 [hp_C]/30 [hp_C]; TURPENTINE OIL 30 [hp_C]/30 [hp_C]; ATROPA BELLADONNA 30 [hp_C]/30 [hp_C]; CAPSELLA BURSA-PASTORIS WHOLE 30 [hp_C]/30 [hp_C]
INACTIVE INGREDIENTS: ALCOHOL 30 [hp_C]/30 [hp_C]

BM184

DOSAGE AND ADMINISTRATION

How to Use

Mix with half a cup of water 3-4 times per day. Ages 12 or older, 10 drops. Ages 12-2, 5 drops. Ages 2 and under, consult your Doctor.

Inactive:

Alcohol Base to Preserve Product

ACTIVE INGREDIENTS

Benzoic acid D10+100C 0.10mL each (HPUS), Buchu D1+10C 0.10mL each (HPUS), Belladonna D10+100C 0.10mL each (HPUS), Terebinthina D1+10C 0.10mL each (HPUS), Thlapsi b.p D1+10C 0.10mL each (HPUS), Triticum rep D1+10C 0.10mL each (HPUS)

Uses
Temporarily relieves discomfort due to bladder issues and excess uric acid, including occasional involuntary urination, burning sensation in the urethra, uneasiness in the bladder, large amounts of colorless urine, and frequent urination.*

Uses
Temporarily relieves discomfort due to bladder issues and excess uric acid, including occasional involuntary urination, burning sensation in the urethra, uneasiness in the bladder, large amounts of colorless urine, and frequent urination.*

KEEP OUT OF REACH OF CHILDREN

Warnings and Storage:

Ask a professional before use if pregnant or breastfeeding or if you have severe symptoms.

Keep away from children. If you have a reaction to this product that is not positive, discontinue use. Store in a cool and dry place

*CLAIMS BASED ON TRADITIONAL HOMEOPATHIC PRACTICE, NOT ACCEPTED MEDICAL EVIDENCE NOT FDA EVALUATED.
This product is not intended to diagnose, treat, cure, or prevent any disease.

Warnings and Storage:

Ask a professional before use if pregnant or breastfeeding or if you have severe symptoms.

Keep away from children. If you have a reaction to this product that is not positive, discontinue use. Store in a cool and dry place

*CLAIMS BASED ON TRADITIONAL HOMEOPATHIC PRACTICE, NOT ACCEPTED MEDICAL EVIDENCE NOT FDA EVALUATED.
This product is not intended to diagnose, treat, cure, or prevent any disease.

Entire package label